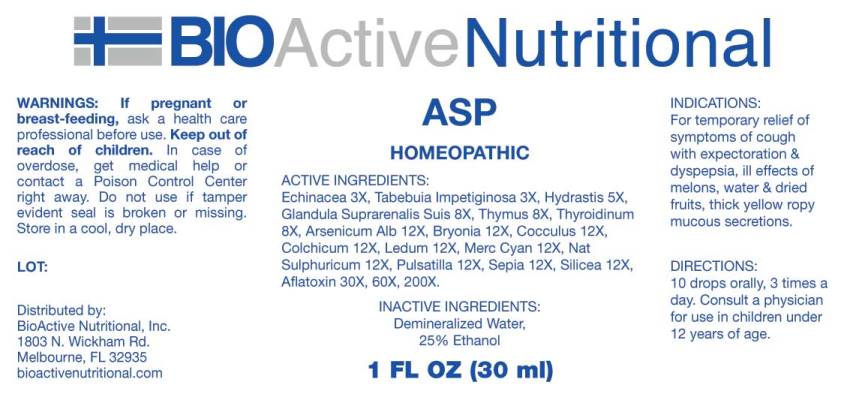 DRUG LABEL: ASP
NDC: 43857-0547 | Form: LIQUID
Manufacturer: BioActive Nutritional, Inc.
Category: homeopathic | Type: HUMAN OTC DRUG LABEL
Date: 20240828

ACTIVE INGREDIENTS: ECHINACEA ANGUSTIFOLIA WHOLE 3 [hp_X]/1 mL; HANDROANTHUS IMPETIGINOSUS BARK 3 [hp_X]/1 mL; GOLDENSEAL 5 [hp_X]/1 mL; SUS SCROFA ADRENAL GLAND 8 [hp_X]/1 mL; SUS SCROFA THYMUS 8 [hp_X]/1 mL; THYROID 8 [hp_X]/1 mL; ARSENIC TRIOXIDE 12 [hp_X]/1 mL; BRYONIA ALBA ROOT 12 [hp_X]/1 mL; ANAMIRTA COCCULUS SEED 12 [hp_X]/1 mL; COLCHICUM AUTUMNALE BULB 12 [hp_X]/1 mL; LEDUM PALUSTRE TWIG 12 [hp_X]/1 mL; MERCURIC CYANIDE 12 [hp_X]/1 mL; SODIUM SULFATE 12 [hp_X]/1 mL; PULSATILLA PRATENSIS WHOLE 12 [hp_X]/1 mL; SEPIA OFFICINALIS JUICE 12 [hp_X]/1 mL; SILICON DIOXIDE 12 [hp_X]/1 mL; AFLATOXIN B1 30 [hp_X]/1 mL
INACTIVE INGREDIENTS: WATER; ALCOHOL

DRUG FACTS:

ACTIVE INGREDIENTS:

Echinacea (Angustifolia) 3X, Tabebuia Impetiginosa 3X, Hydrastis Canadensis 5X, Glandula Suprarenalis Suis 8X, Thymus (Suis) 8X, Thyroidinum (Suis) 8X, Arsenicum Album 12X, Bryonia (Alba) 12X, Cocculus Indicus 12X, Colchicum Autumnale 12X, Ledum Palustre 12X, Mercurius Cyanatus 12X, Natrum Sulphuricum 12X, Pulsatilla (Pratensis) 12X, Sepia 12X, Silicea 12X, Aflatoxin (B1) 30X, 60X, 200X.

INDICATIONS:

For temporary relief of symptoms of cough with expectoration & dyspepsia, ill effects of melons, water & dried fruits, thick yellow ropy mucous secretions.

WARNINGS:

If pregnant or breast-feeding, ask a health care professional before use.

Keep out of reach of children. In case of overdose, get medical help or contact a Poison Control Center right away.

Do not use if tamper evident seal is broken or missing.

Store in cool, dry place.

Keep out of reach of children. In case of overdose, get medical help or contact a Poison Control Center right away.

DIRECTIONS:

10 drops orally, 3 times a day. Consult a physician for use in children under 12 years of age.

INDICATIONS:

For temporary relief of symptoms of cough with expectoration & dyspepsia, ill effects of melons, water & dried fruits, thick yellow ropy mucous secretions.

INACTIVE INGREDIENTS:

Demineralized Water, 25% Ethanol

QUESTIONS:

Distributed by:
BioActive Nutritional, Inc.
1803 N. Wickham Rd.
Melbourne, FL 32935
bioactivenutritional.com

PACKAGE LABEL DISPLAY:

BIOActive Nutritional

ASP

HOMEOPATHIC

1 FL OZ (30 ml)